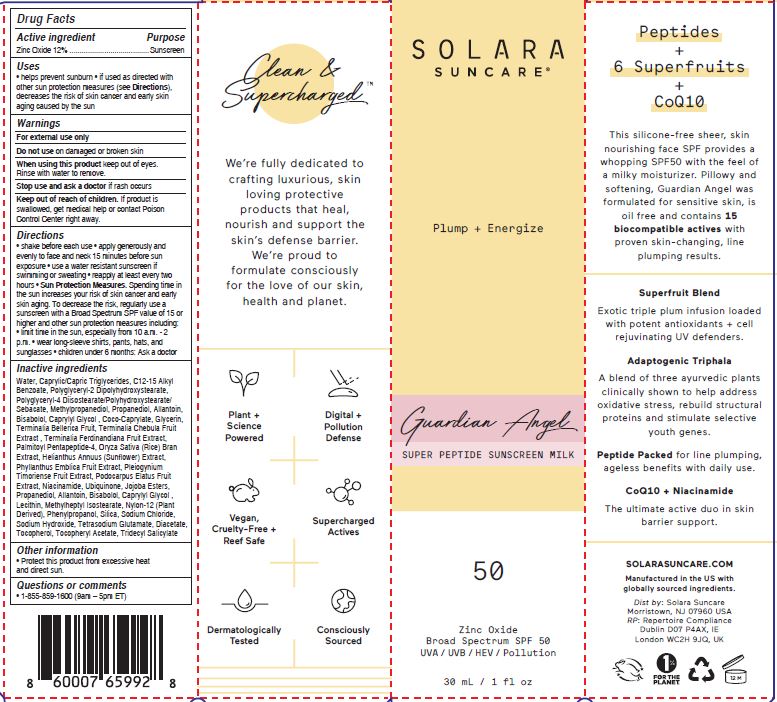 DRUG LABEL: GUARDIAN ANGEL SUPER PEPTIDE SUNSCREEN MILK

NDC: 73054-126 | Form: LOTION
Manufacturer: SOLARA SUNCARE, INC.
Category: otc | Type: HUMAN OTC DRUG LABEL
Date: 20251222

ACTIVE INGREDIENTS: ZINC OXIDE 12 g/100 mL
INACTIVE INGREDIENTS: COCO-CAPRYLATE; TOCOPHEROL; PHYLLANTHUS EMBLICA FRUIT JUICE; PHENYLPROPANOL; ALKYL (C12-15) BENZOATE; MEDIUM-CHAIN TRIGLYCERIDES; POLYGLYCERYL-4 DIISOSTEARATE/POLYHYDROXYSTEARATE/SEBACATE; NIACINAMIDE; NYLON-12; SILICON DIOXIDE; TRIDECYL SALICYLATE; PALMITOYL PENTAPEPTIDE-4; TERMINALIA BELLIRICA FRUIT; KAKADU PLUM; SODIUM HYDROXIDE; TETRASODIUM GLUTAMATE DIACETATE; TERMINALIA CHEBULA FRUIT; RICE BRAN; METHYLHEPTYL ISOSTEARATE; METHYLPROPANEDIOL; LEVOMENOL; .ALPHA.-TOCOPHEROL ACETATE; POLYGLYCERYL-2 DIPOLYHYDROXYSTEARATE; PODOCARPUS ELATUS FRUIT; UBIDECARENONE; LECITHIN, SUNFLOWER; WATER; GLYCERIN; HYDROLYZED JOJOBA ESTERS (ACID FORM); GLYCYRRHIZINATE DIPOTASSIUM; HELIANTHUS ANNUUS FLOWERING TOP; ALLANTOIN; CAPRYLYL GLYCOL; PROPANEDIOL; PLEIOGYNIUM TIMORIENSE FRUIT; SODIUM CHLORIDE

SOLARA (as PLD) - GUARDIAN ANGEL SUPER PEPTIDE SUNSCREEN MILK SPF-50 (73054-126)

ACTIVE INGREDIENT

Zinc Oxide 12%

PURPOSE

Sunscreen

USES

- helps prevent sunburn
- if used as directed with other sun protection measures (see Directions), decreases the risk of skin cancer and early skin aging caused by the sun

Keep out of reach of children. If product is swallowed, get medical help or contact Poison Control Center right away.

WARNINGS

FOR EXTERNAL USE ONLY

DO NOT USE ON DAMAGED OR BROKEN SKIN

WHEN USING THIS PRODUCT KEEP OUT OF EYES. RINSE WITH WATER TO REMOVE.

STOP USE AND ASK A DOCTOR IF RASH OCCURS

DIRECTIONS

- shake or knead before each use
- apply generously and evenly 15 minutes before sun exposure
- use a water-resistant sunscreen if swimming or sweating
- reapply at least every two hours

- Sun Protection Measures. Spending time in the sun increases your risk of skin cancer and early skin aging. To decrease the risk, regularly use asunscreen with a Broad Spectrum SPF value of 15 or higher and other sun protection measures including:
- limit time in the sun, especially from 10 a.m. - 2 p.m.
- wear long-sleeve shirts, pants, hats, and sunglasses
- children under 6 months: Ask a doctor

INACTIVE INGREDIENTS

Water (Aqua), C12-15 Alkyl Benzoate, Caprylic/Capric Triglycerides, Jojoba Esters, Propanediol, Tridecyl Salicylate, Methylheptyl Isostearate, Polyglyceryl-4 Diisostearate/Polyhydroxystearate/Sebacate, Niacinamide, Methylpropanediol, Nylon-12 (Plant Derived), Glycerin, Silica, Palmitoyl Pentapeptide-4, Terminalia Bellerica Fruit, Terminalia Chebula Fruit Extract, Terminalia Ferdinandiana Fruit Extract, Phyllanthus Emblica Fruit Extract, Pleiogynium Timoriense Fruit Extract, Podocarpus Elatus Fruit Extract, Ubiquinone, Helianthus Annuus (Sunflower) Extract, Oryza Sativa (Rice) Bran Extract, Propanediol, Allantoin, Bisabolol, Caprylyl Glycol, Lecithin, Caprylyl Glycol, Coco-Caprylate, Phenylpropanol, Sodium Chloride, Sodium Hydroxide, Tetrasodium Glutamate, Diacetate, Tocopherol, Tocopheryl Acetate, Polyglyceryl-2 Dipolyhydroxystearate

OTHER INFORMATION

- Protect this product from excessive heat and direct sun.

QUESTIONS OR COMMENTS

- 1-855-859-1600 (9am – 5pm ET)